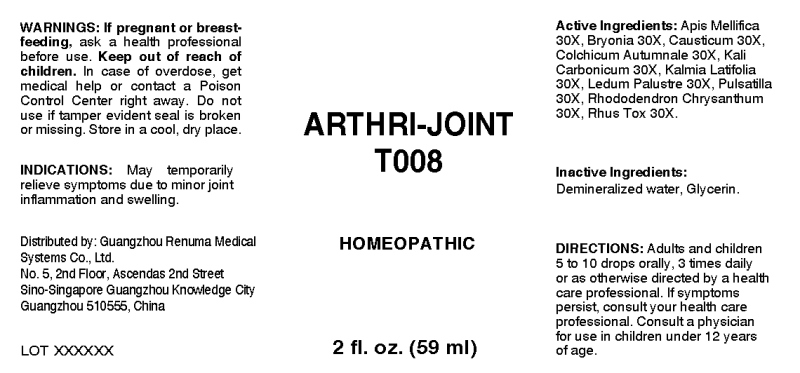 DRUG LABEL: Arthri-Joint
NDC: 71742-0002 | Form: LIQUID
Manufacturer: Guangzhou Renuma Medical Systems Co., Ltd
Category: homeopathic | Type: HUMAN OTC DRUG LABEL
Date: 20171023

ACTIVE INGREDIENTS: APIS MELLIFERA 30 [hp_X]/1 mL; BRYONIA ALBA ROOT 30 [hp_X]/1 mL; CAUSTICUM 30 [hp_X]/1 mL; COLCHICUM AUTUMNALE BULB 30 [hp_X]/1 mL; POTASSIUM CARBONATE 30 [hp_X]/1 mL; KALMIA LATIFOLIA LEAF 30 [hp_X]/1 mL; LEDUM PALUSTRE TWIG 30 [hp_X]/1 mL; PULSATILLA VULGARIS 30 [hp_X]/1 mL; RHODODENDRON AUREUM LEAF 30 [hp_X]/1 mL; TOXICODENDRON PUBESCENS LEAF 30 [hp_X]/1 mL
INACTIVE INGREDIENTS: WATER; GLYCERIN

Drug Facts:

ACTIVE INGREDIENTS:

Apis Mellifica 30X, Bryonia (Alba) 30X, Causticum 30X, Colchicum Autumnale 30X, Kali Carbonicum 30X, Kalmia Latifolia 30X, Ledum Palustre 30X, Pulsatilla (Vulgaris) 30X, Rhododendron Chrysanthum 30X, Rhus Tox 30X.

INDICATIONS:

May temporarily relieve symptoms due to minor joint inflammation and swelling.

WARNINGS:

If pregnant or breast-feeding, ask a health care professional before use.
Keep out of reach of children. In case of overdose, get medical help or contact a Poison Control Center right away.
Do not use if tamper evident seal is broken or missing.
Store in cool, dry place.

Keep out of reach of children. In case of overdose, get medical help or contact a Poison Control Center right away.

DIRECTIONS:

Adults and children 5 to 10 drops orally, 1 to 2 times daily or as otherwise directed by a health care professional. If symptoms persist, consult your health care professional. Consult a physician for use in children under 12 years of age.

INDICATIONS:

May temporarily relieve symptoms due to minor joint inflammation and swelling.

INACTIVE INGREDIENTS:

Demineralized water, Glycerin

QUESTIONS:

Distributed by:
Guangzhou Renuma Medical
Systems Co., Ltd.
No. 5, 2nd Floor, Ascendas 2nd Street
Sino-Singapore Guangzhou Knowledge City
Guangzhou 510555, China

PACKAGE LABEL DISPLAY:

ARTHRI-JOINT

T008

HOMEOPATHIC

2 fl. oz. (59 ml)